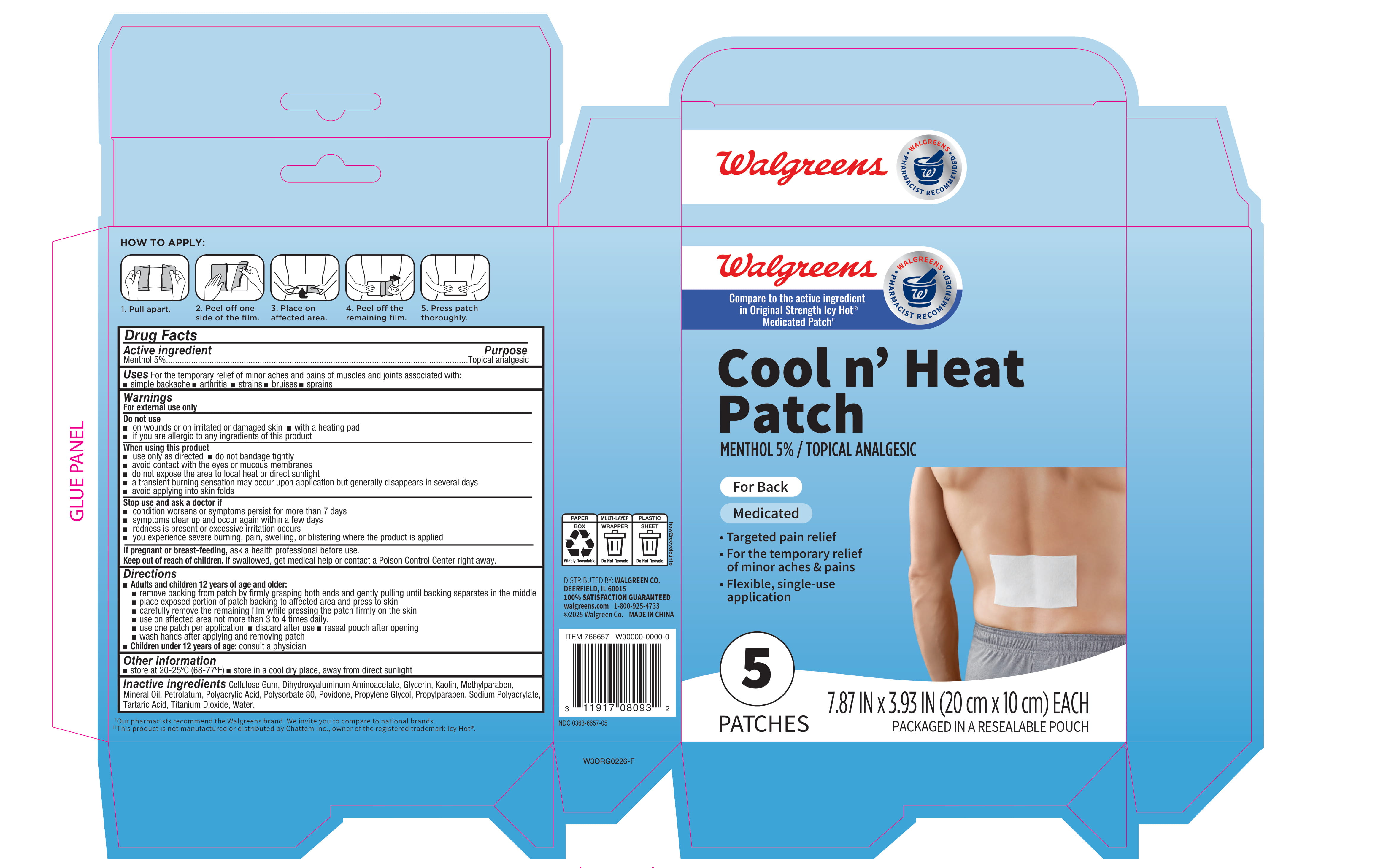 DRUG LABEL: Walgreens Cool N Heat Back Patch
NDC: 0363-6657 | Form: PATCH
Manufacturer: Walgreen Co.
Category: otc | Type: HUMAN OTC DRUG LABEL
Date: 20260210

ACTIVE INGREDIENTS: MENTHOL 50 mg/1 g
INACTIVE INGREDIENTS: MINERAL OIL; GLYCERIN; PETROLATUM; PROPYLENE GLYCOL; PROPYLPARABEN; SODIUM POLYACRYLATE (8000 MW); TARTARIC ACID; KAOLIN; POVIDONE; POLYACRYLIC ACID (8000 MW); TITANIUM DIOXIDE; METHYLPARABEN; WATER; DIHYDROXYALUMINUM AMINOACETATE; CELLULOSE GUM; POLYSORBATE 80

Walgreens Cool n Heat Patch 766657

Active ingredient

Menthol 5%

Purpose

Topical analgesic

Uses

For the temporary relief of minor aches and pains of muscles and joints associated with:

- simple backache
- arthritis
- strains
- bruises
- sprains

Warnings

For external use only

Do not use

- on wounds or on irritated or damaged skin
- with a heating pad
- if you are allergic to any ingredients of this product

When using this product

- use only as directed
- do not bandage tightly
- avoid contact with the yes or mucous membranes
- do not expose the area to local heat or direct sunlight
- a transient burning sensation may occur upon application but generally disappears in several days
- avoid applying into skin folds

Stop use and ask a doctor if

- condition worsens or symptoms persist for more than 7 days
- symptoms clear up and occur again within a few days
- redness is present or excessive irritation occurs
- you experience severe burning, pain, swelling, or blistering where the product is applied

If pregnant or breast-feeding,

ask a health professional before use.

Keep out of reach of children.

If swallowed, get medical help or contact a Poison Control Center right away.

Directions

- Adults and children 12 years of age and older:
- remove backing from patch by firmly grasping both ends and gently pulling until backing separates in the middle
- place exposed portion of patch backing to affected area and press to skin
- carefully remove the remaining film while pressing the patch firmly on the skin
- use on affected area not more than 3 to 4 times daily.
- use one patch per application
- discard after use
- reseal pouch after opening
- wash hands after applying and removing patch
- Children under 12 years of age: consult a physician

Other information

- store at 20-25°C (68-77°F)
- store in a cool dry place, away from direct sunlight

Inactive ingredients

Cellulose Gum, Dihydroxyaluminum Aminoacetate, Glycerin, Kaolin, Methylparaben, Mineral Oil, Petrolatum, Polyacrylic Acid, Polysorbate 80, Povidone, Propylene Glycol, Propylparaben, Sodium Polyacrylate, Tartaric Acid, Titanium Dioxide, Water.

Principal Display Panel - 7.87 IN x 3.93 IN Carton Label

Walgreens

Compare to the active ingredient in Original Strength Icy Hot® Medicated Patch

Cool n' Heat

Patch

Menthol 5% / Topical Analgesic

For Back

Medicated

- Targeted pain relief
- For the temporary relief of minor aches & pains
- Flexible, single-use application

5 PATCHES

7.87 IN x 3.93 IN (20 cm x 10 cm) EACH

Packaged in a resealable pouch